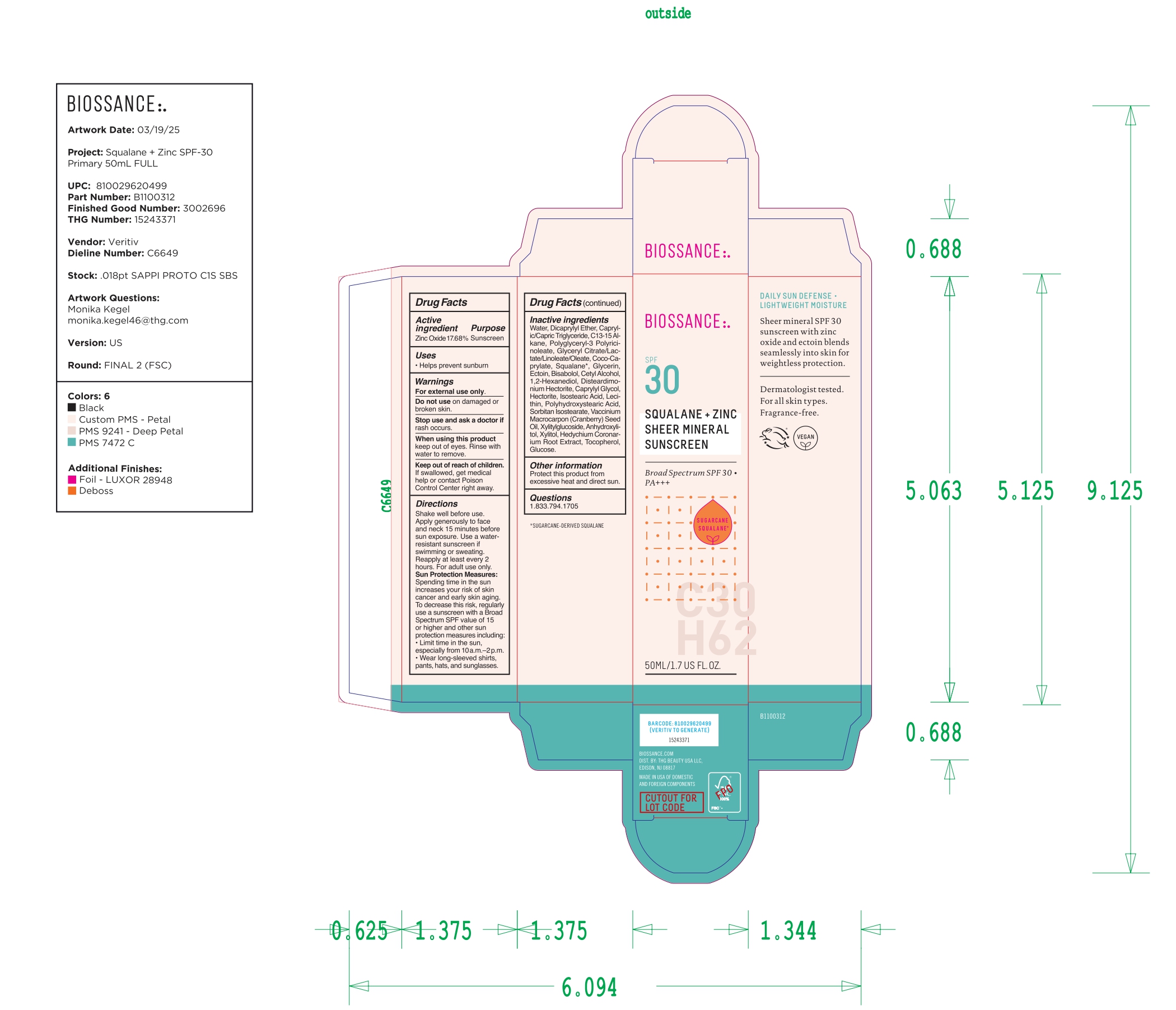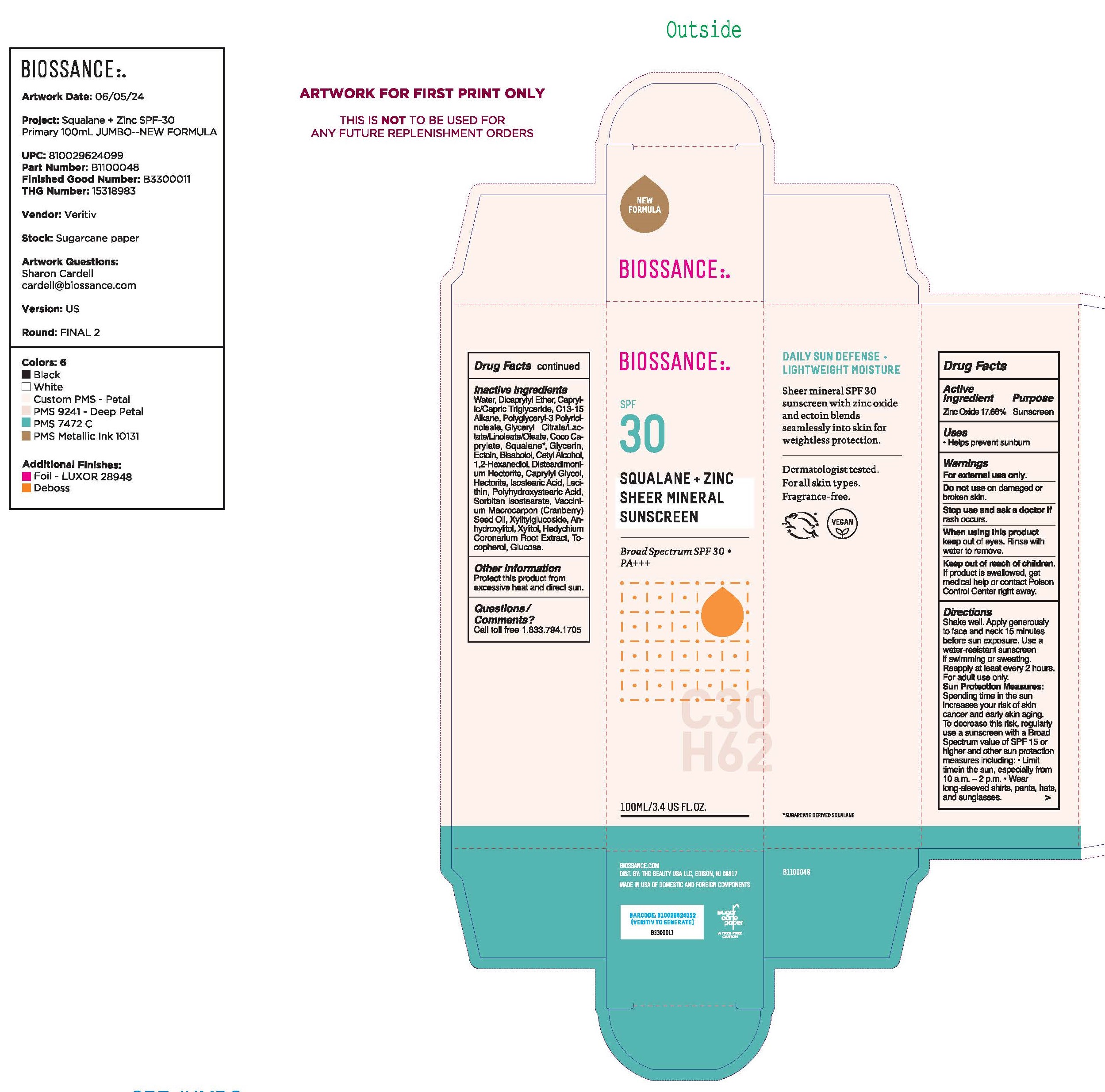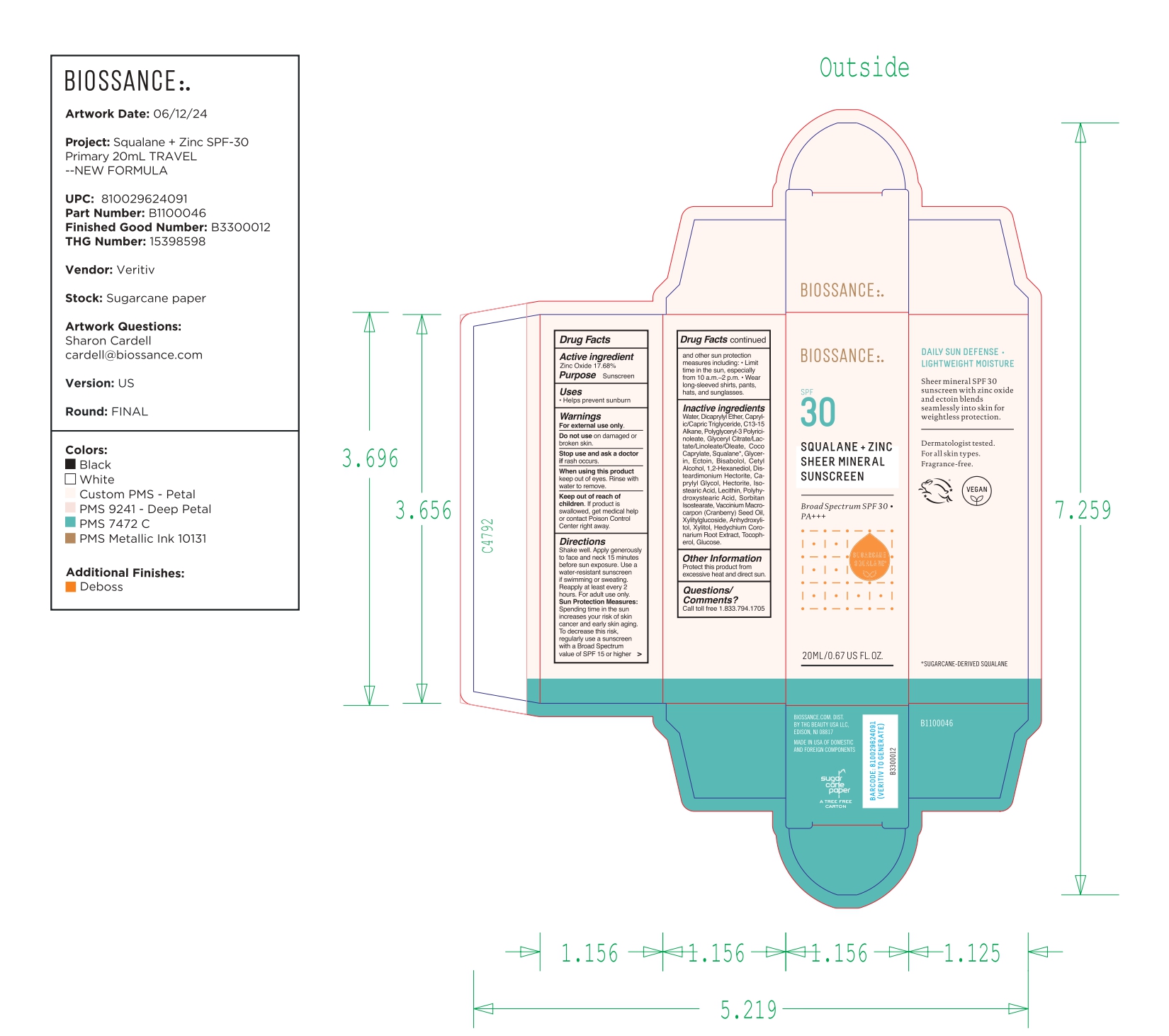 DRUG LABEL: Biossance Squalane and Zinc Sheer Mineral Sunscreen Broad Spectrum SPF 30
NDC: 84448-344 | Form: CREAM
Manufacturer: THG Beauty USA LLC
Category: otc | Type: HUMAN OTC DRUG LABEL
Date: 20251029

ACTIVE INGREDIENTS: ZINC OXIDE 17.68 g/100 mL
INACTIVE INGREDIENTS: TOCOPHEROL; CAPRYLIC/CAPRIC TRIGLYCERIDE; GLYCERYL CITRATE/LACTATE/LINOLEATE/OLEATE; WATER; DICAPRYLYL ETHER; C13-15 ALKANE; POLYGLYCERYL-3 PENTARICINOLEATE; GLYCERIN; 1,2-HEXANEDIOL; DISTEARDIMONIUM HECTORITE; ISOSTEARIC ACID; SQUALANE; BISABOLOL; LECITHIN, SOYBEAN; POLYHYDROXYSTEARIC ACID (2300 MW); SORBITAN ISOSTEARATE; COCO-CAPRYLATE; VACCINIUM MACROCARPON (CRANBERRY) SEED OIL; ANHYDROXYLITOL; XYLITOL; HEDYCHIUM CORONARIUM ROOT; GLUCOSE; HECTORITE; ECTOINE; CETYL ALCOHOL; CAPRYLYL GLYCOL; XYLITYLGLUCOSIDE

ACTIVE INGREDIENT

Zinc Oxide 17.68%

PURPOSE

Sunscreen

INDICATIONS AND USAGE

Helps prevent sunburn.

WARNINGS

For external use only.

Do not use on damaged or broken skin.

When using this product keep out of eyes. Rinse with water to remove.

Stop use and ask a doctor if rash occurs.

Keep out of reach of children. If swallowed, get medical help or contact a Poison Control Center right away.

DOSAGE AND ADMINISTRATION

Shake well. Apply generously to face and neck 15 minutes before sun exposure. Use a water resistant sunscreen if swimming or sweating. Reapply at least every 2 hours. For adult use only.

Sun Protection Measures: Spending time in the sun increases your risk of skin cancer and early skin aging. To decrease this risk, regularly use a sunscreen with a Broad Spectrum SPF value of 15 or higher and other sun protection measures including: ■ limit time in the sun, especially from 10 a.m.-2p.m ■ wear long-sleeved shirts, pants, hats, and sunglasses.

OTHER SAFETY INFORMATION

Protect this product from excessive heat and direct sun.

INACTIVE INGREDIENT

WATER, DICAPRYLYL ETHER, CAPRYLIC/CAPRIC TRIGLYCERIDE, C13-15 ALKANE, POLYGLYCERYL-3 POLYRICINOLEATE, GLYCERYL CITRATE/LACTATE/LINOLEATE/OLEATE, COCO-CAPRYLATE, SQUALANE, GLYCERIN, ECTOIN, BISABOLOL, CETYL ALCOHOL, 1,2-HEXANEDIOL, DISTEARDIMONIUM HECTORITE, CAPRYLYL GLYCOL, HECTORITE, ISOSTEARIC ACID, LECITHIN, POLYHYDROXYSTEARIC ACID, SORBITAN ISOSTEARATE, VACCINIUM MACROCARPON (CRANBERRY) SEED OIL, XYLITYLGLUCOSIDE, ANHYDROXYLITOL, XYLITOL, HEDYCHIUM CORONARIUM ROOT EXTRACT, TOCOPHEROL, GLUCOSE.

QUESTIONS

1 833 794 1705